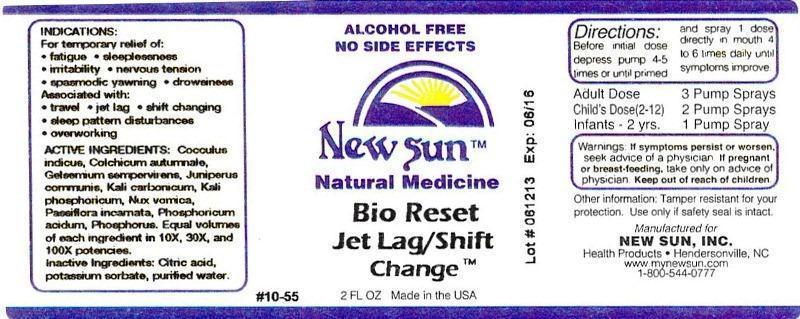 DRUG LABEL: Bio Reset Jet Lag/Shift Change
NDC: 66579-0055 | Form: LIQUID
Manufacturer: New Sun Inc.
Category: homeopathic | Type: HUMAN OTC DRUG LABEL
Date: 20141024

ACTIVE INGREDIENTS: ANAMIRTA COCCULUS SEED 10 [hp_X]/59 mL; COLCHICUM AUTUMNALE BULB 10 [hp_X]/59 mL; GELSEMIUM SEMPERVIRENS ROOT 10 [hp_X]/59 mL; JUNIPER BERRY 10 [hp_X]/59 mL; POTASSIUM CARBONATE 10 [hp_X]/59 mL; POTASSIUM PHOSPHATE, DIBASIC 10 [hp_X]/59 mL; STRYCHNOS NUX-VOMICA SEED 10 [hp_X]/59 mL; PASSIFLORA INCARNATA FLOWERING TOP 10 [hp_X]/59 mL; PHOSPHORIC ACID 10 [hp_X]/59 mL; PHOSPHORUS 10 [hp_X]/59 mL
INACTIVE INGREDIENTS: CITRIC ACID MONOHYDRATE; POTASSIUM SORBATE; WATER

Bio Reset Jet Lag/Shift

DOSAGE AND ADMINISTRATION

Directions: Before initial dose depress pump 4-5 times or until primed and spray 1 dose directly in mouth 4 to 6 times daily until symptoms improve.

Adult Dose: 3 Pump Sprays

Child's Dose (2-12): 2 Pump Sprays

Infants - 2 yrs. 1 Pump Spray

WARNINGS

Warnings: If symptoms persist or worsen, seek advice of a physician. If pregnant or breast-feeding, take only on advice of physician.

Keep out of reach of children.

Other information: Tamper resistant for your protection. Use only if safety seal is intact.

PURPOSE

Indications: For temporary relief of: •fatigue •sleeplessness •irritability •nervous tension •spasmodic yawning •drowsiness

Associated with: •travel •jet lag •shift changing •sleep pattern disturbances •overworking

ACTIVE INGREDIENT

Active Ingredients: Cocculus indicus, Colchicum autumnale, Gelsemium sempervirens, Juniperus communis, Kali carbonicum, Kali phosphoricum, Nux vomica, Passiflora incarnata, Phosphoricum acidum, Phosphorus. Equal volumes of each ingredient in 10X, 30X, and 100X potencies.

Inactive Ingredient: Citric acid, potassium sorbate, purified water.

Indications: For temporary relief of:

- fatigue
- sleeplessness
- irritability
- nervous tension
- spasmodic yawning
- drowsiness
- travel
- jet lag
- shift changing
- sleep pattern disturbances
- overworking